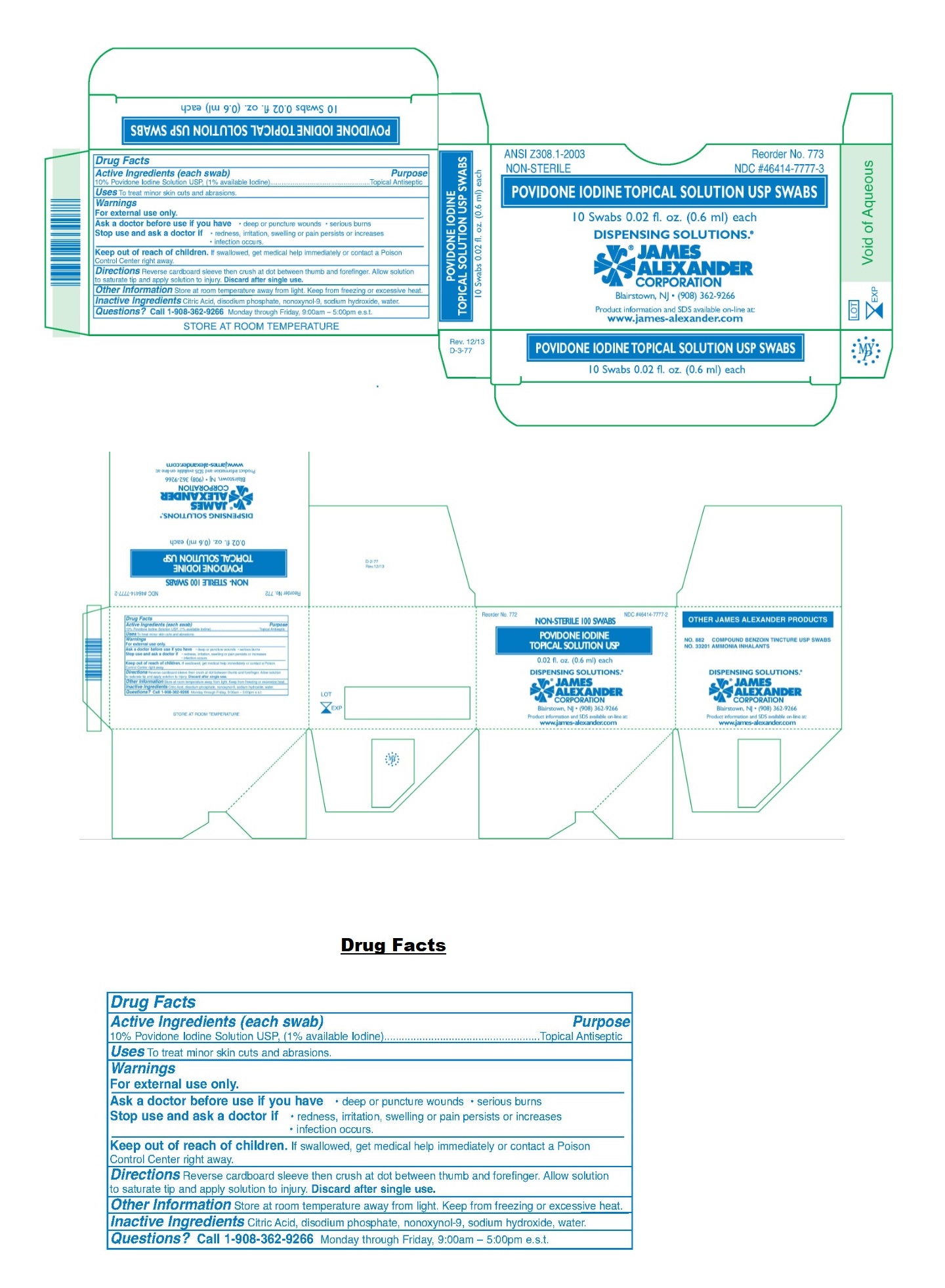 DRUG LABEL: POVIDONE-IODINE
NDC: 46414-7777 | Form: SOLUTION
Manufacturer: James Alexander Corporation
Category: otc | Type: HUMAN OTC DRUG LABEL
Date: 20251023

ACTIVE INGREDIENTS: POVIDONE-IODINE 10 mg/1 mL
INACTIVE INGREDIENTS: CITRIC ACID MONOHYDRATE; SODIUM PHOSPHATE, DIBASIC, ANHYDROUS; NONOXYNOL-9; SODIUM HYDROXIDE; WATER

POVIDONE IODINE TOPICAL SOLUTION USP

Active Ingredients (each swab)

10% Povidone Iodine Solution USP, (1% available Iodine)

Purpose

Topical Antiseptic

Uses

To treat minor skin cuts and abrasions.

Warnings

For external use only.

Ask a doctor before use if you have • deep or puncture wounds • serious burns

Stop use and ask a doctor if • redness, irritation, swelling or pain persists or increases
• infection occurs.

Keep out of reach of children. If swallowed, get medical help immediately or contact a Poison Control Center right away.

Directions

Reverse cardboard sleeve then crush at dot between thumb and forefinger. Allow solution to saturate tip and apply solution to injury. Discard after single use.

Other Information

Store at room temperature away from light. Keep from freezing or excessive heat.

Inactive Ingredients

Citric acid, disodium phosphate, nonoxynol-9, sodium hydroxide, water.

Questions?

Call 1-908-362-9266 Monday through Friday, 9:00am - 5:00pm e.s.t.

DISPENSING SOLUTIONS®

JAMES ALEXANDER CORPORATION
Blairstown, NJ• (908) 362-9266
Product information and MSDS available on-line at:
www.james-alexander.com

Void of Aqueous